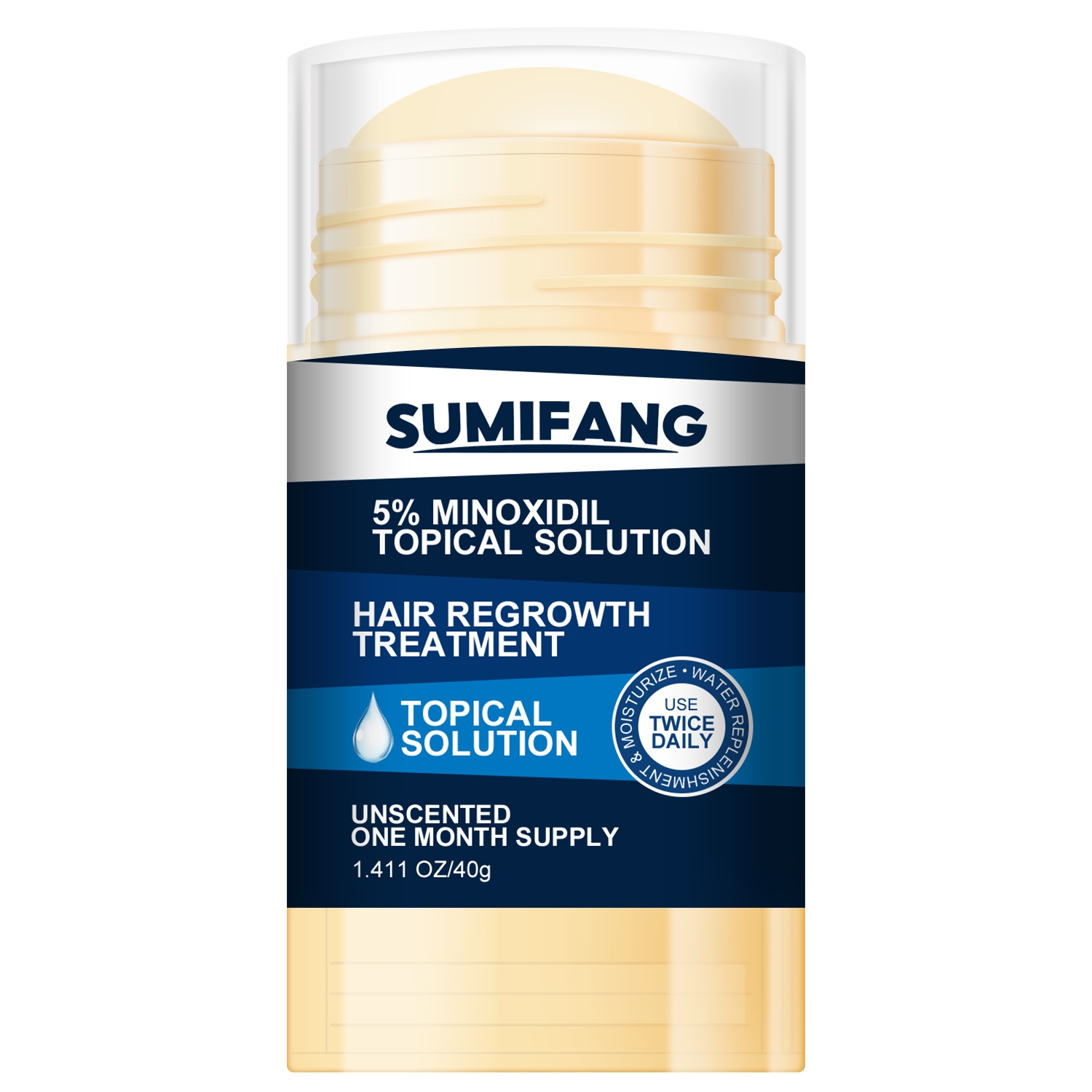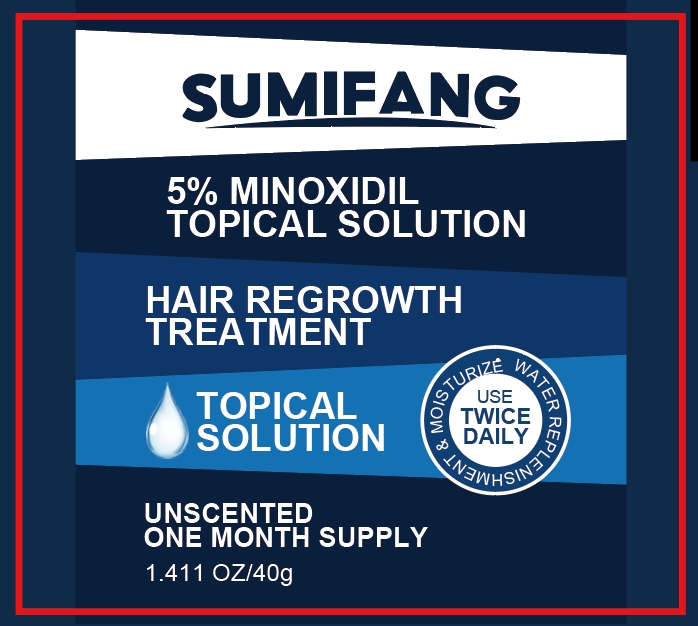 DRUG LABEL: Beard cream
NDC: 84025-119 | Form: CREAM
Manufacturer: Guangzhou Yanxi Biotechnology Co.. Ltd
Category: otc | Type: HUMAN OTC DRUG LABEL
Date: 20240806

ACTIVE INGREDIENTS: CETEARYL OLIVATE 3 mg/40 g; NIACINAMIDE 5 mg/40 g
INACTIVE INGREDIENTS: WATER

DOSAGE AND ADMINISTRATION

Cream for beard care and maintenance of healthy beard growth

WARNINGS

Keep out of children

INACTIVE INGREDIENT

Aqua

INDICATIONS AND USAGE

For the daily care of men's beards

Keep out of children

PURPOSE

Promotes beard hair growth and maintains healthy beard growth